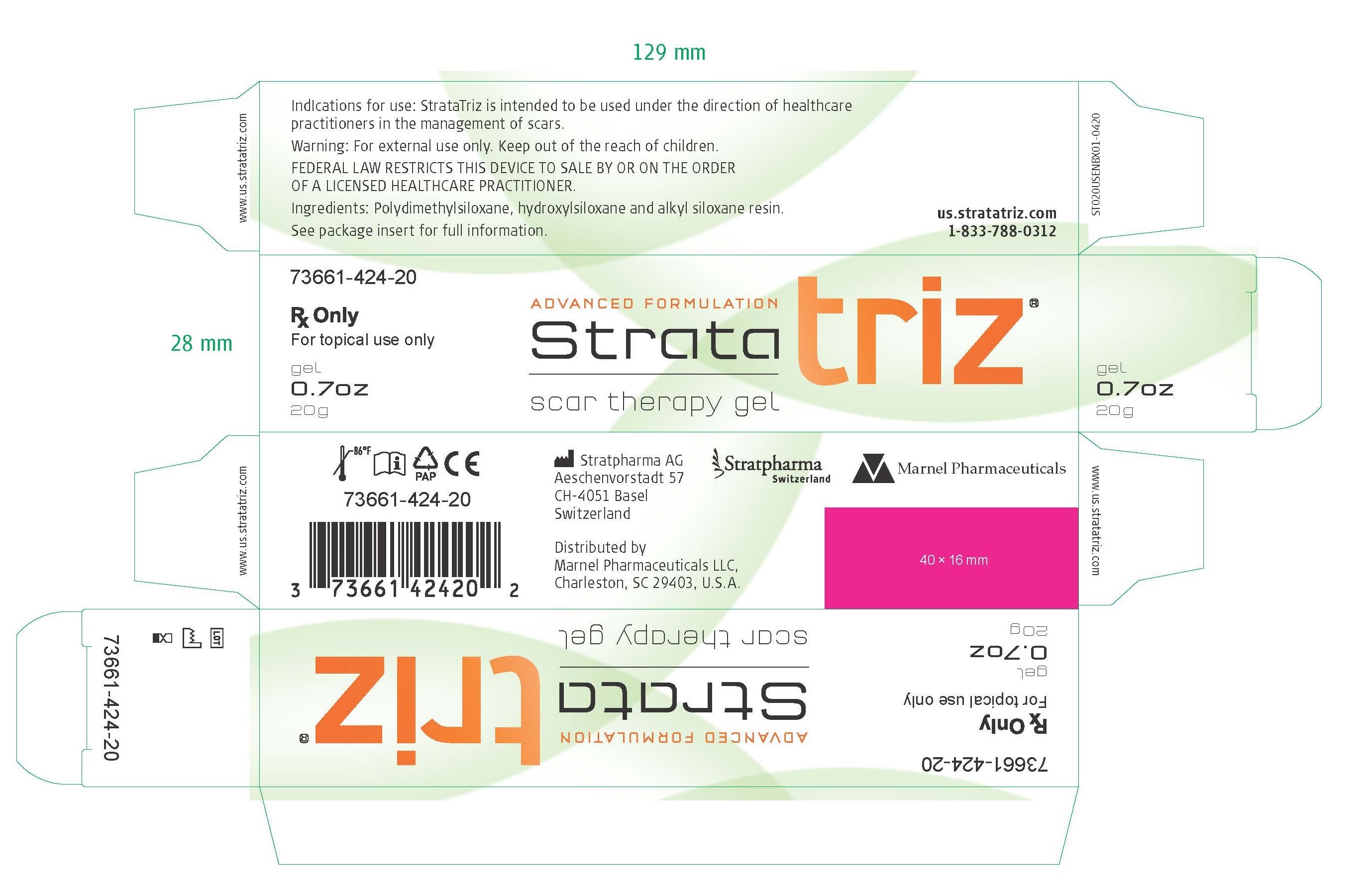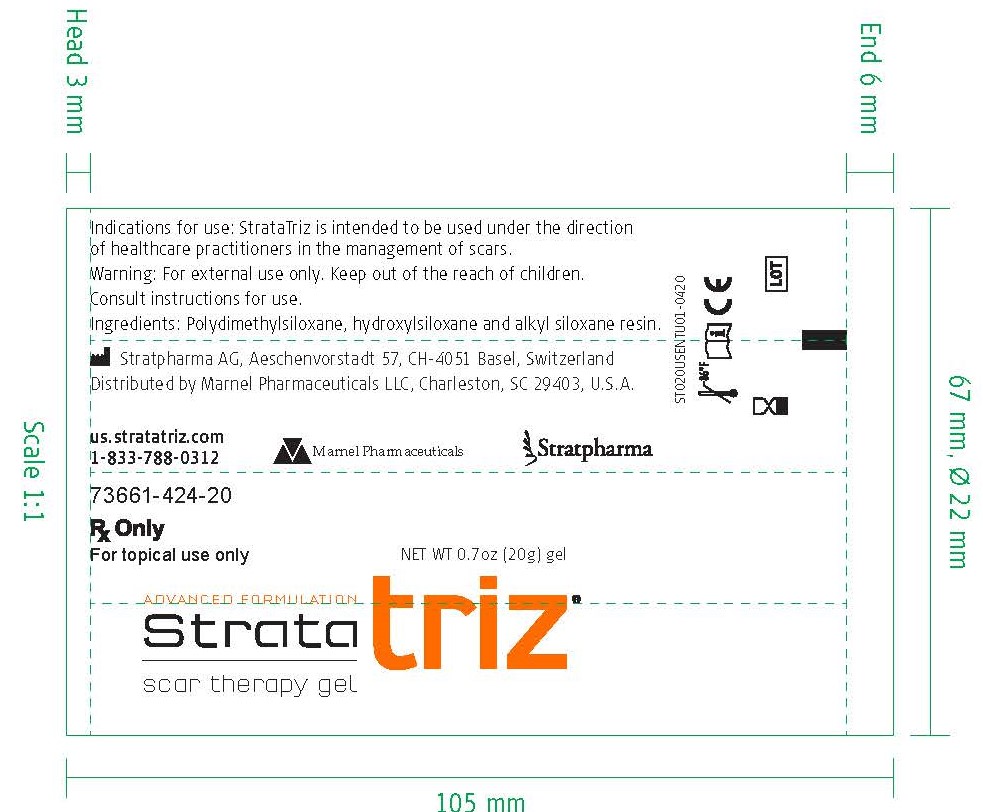 DRUG LABEL: StrataTriz
NDC: 73661-424
Manufacturer: Marnel Pharmaceuticals, Inc.
Category: other | Type: MEDICAL DEVICE
Date: 20200715
INACTIVE INGREDIENTS: DIMETHICONE; DIMETHICONOL (2000 CST); CAPRYLYL TRISILOXANE

StrataTriz

WARNINGS AND PRECAUTIONS

Rx Only

For topical use only

Federal Law restricts this device to sale by or on the order of a licensed healthcare practitioner.

[EN] Description

StrataTriz is a transparent gel formulation for the management of scars, both old and new.

When used as directed StrataTriz dries to form a protective layer that is gas permeable and waterproof which hydrates and protects scars from chemical and microbial invasion, allowing scars to normalize the collagen synthesis cycles, producing a normal mature scar.

StrataTriz is suitable for all areas of the skin, including exposed areas like the face and neck as well as joints and hairy areas without the need for shaving.

INDICATIONS AND USAGE

Indication for use

StrataTriz is intended to be used under the direction of healthcare practitioners in the management of scars.

StrataTriz is indicated for the use on all types of scars including those resulting from:

- general and cosmetic surgery
- trauma
- chronic wounds
- burns
- bites
- acne, and other diseases of the skin.

StrataTriz is indicated to soften and flatten scars, relieve the itching and discomfort as well as to reduce redness and discoloration associated with scars.

StrataTriz is used for the topical management of keloids and hypertrophic scars.

It contains no alcohols, parabens or fragrances.

StrataTriz is suitable for children or people with sensitive skin.

StrataTriz is suitable to use on infants, during pregnancy and whilst breast-feeding.

StrataTriz is intended for single patient use.

On first use of 0.7 oz (20g) tubes remove the cap, cut the nozzle tip of the tube and close with the cap after use.

INDICATIONS AND USAGE

Directions for use

Ensure that the scar is clean and dry.

Apply a very thin layer of StrataTriz to the scar and allow to dry.

When applied correctly, StrataTriz should be dry in 3-4 minutes.

If it takes longer to dry you have probably applied too much. Gently remove the excess with a tissue and allow the drying process to continue.

Once dry, StrataTriz can be covered with sunscreen, cosmetics, pressure garments or casts.

StrataTriz should be applied once daily, or twice daily to exposed areas or as advised by your physician.

For best results StrataTriz should be maintained in continuous contact with the skin (24 hours a day/7 days a week).

PATIENT COUNSELING INFORMATION

How much StrataTriz do I need?

StrataTriz gel is an advanced formulation that requires substantially less product per application than typical creams or gels.

StrataTriz 0.7 oz (20g) is enough to treat an area of 5x5 inch (12x12cm) twice per day for 30 days.

Warning

- For external use only.
- StrataTriz should not be applied on third degree burns or to open wounds.
- StrataTriz should not be placed in contact with mucous membranes or the eyes.
- StrataTriz should not be applied over topical medications unless advised by your physician.
- StrataTriz may stain clothing if not completely dry. If staining occurs, dry cleaning should be able to remove it without damaging the fabric.
- For correct storage please reclose the tube tightly with the cap.
- If irritation occurs, discontinue use and consult your physician.
- Keep out of the reach of children.
- Do not use after the expiration (EXP) date printed on the tube. The expiration (EXP) date does not change once the tube has been opened.
- Do not use if the tube is damaged.

Contraindications

Do not administer to patients with known hypersensitivity to the ingredients of this product.

Ingredients: Polydimethylsiloxane, hydroxysiloxane and alkyl siloxane resin.

How supplied:

StrataTriz 0.7 oz (20g) tube

Product identification code:

73661-424-20